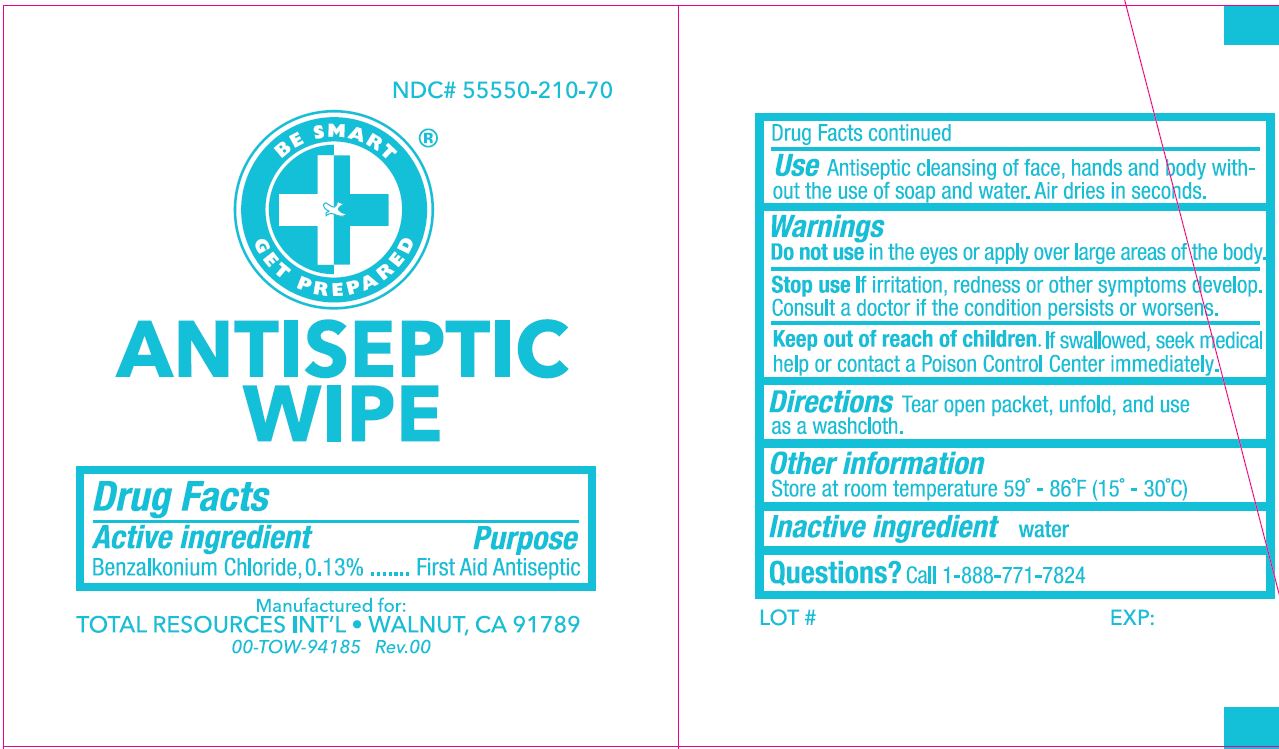 DRUG LABEL: Antiseptic Wipe
NDC: 55550-210 | Form: LIQUID
Manufacturer: Total Resources
Category: otc | Type: HUMAN OTC DRUG LABEL
Date: 20221118

ACTIVE INGREDIENTS: BENZALKONIUM CHLORIDE 0.13 mg/1 mg
INACTIVE INGREDIENTS: WATER 1 mg/1 mg

TR-1331 NDC 55550-210-70
Antiseptic Wipe

Active ingredient

Benzalkonium Chloride, 0.13%

Purpose

First Aid Antiseptic

Use

Antiseptic cleansing of face, hands and body without the use of soap and water. Air dries in seconds.

Warnings

Do not use in the eyes or apply over large areas of the body.

Stop use if

irritation, redness or other symptoms develop. Cosult a doctor if the condition persists or worsens.

KEEP OUT OF REACH OF CHILDREN

If swallowed, seek medical help or contact a Poison Control Center immediately.

Directions

Tear open packet, unfold, and use as a washcloth.

Other information

Store at room temperature 59° - 86°F (15° - 30°C)

Inactive ingredient

water

Questions?

Call 1-888-771-7824